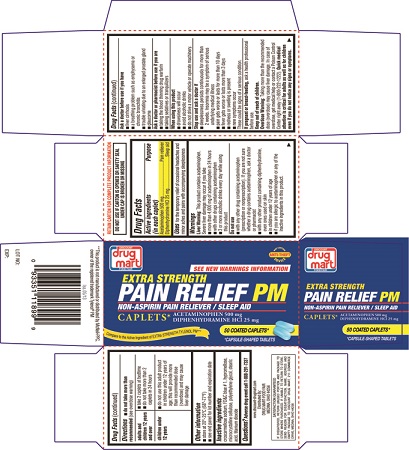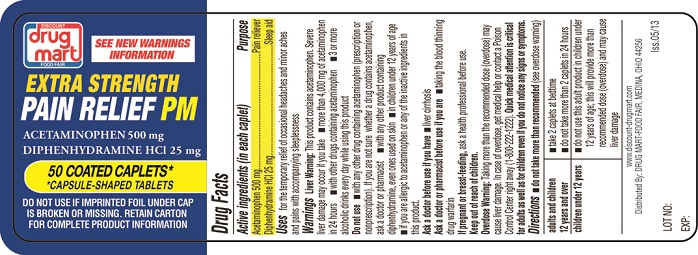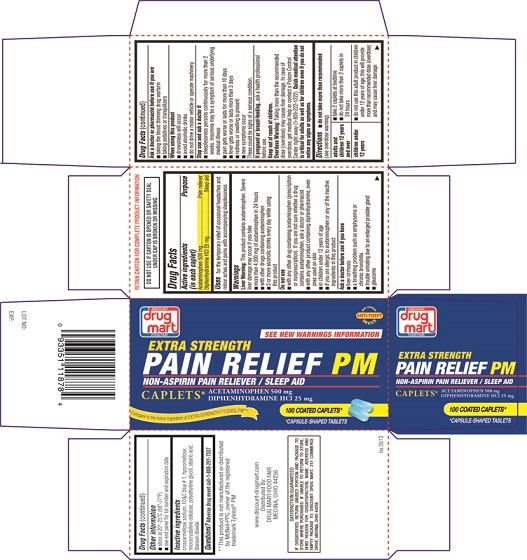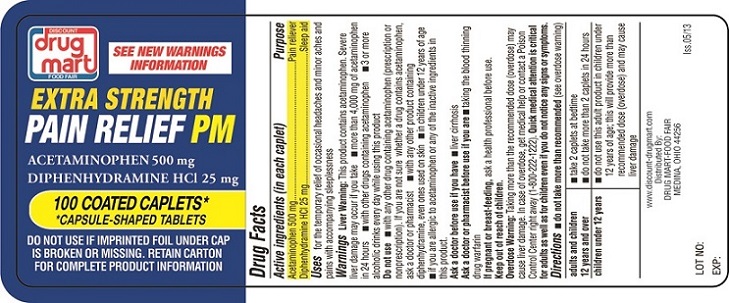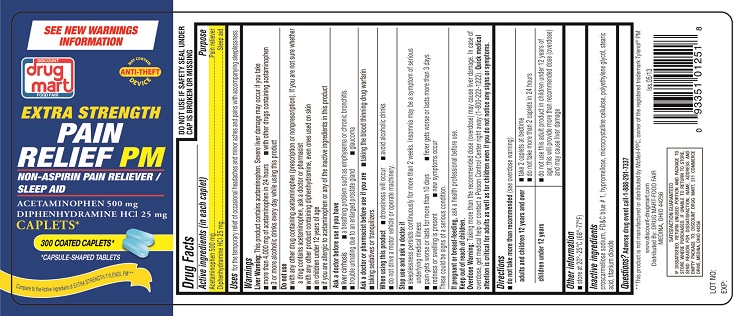 DRUG LABEL: Extra Strength Pain Relief PM
NDC: 53943-024 | Form: TABLET, COATED
Manufacturer: Discount Drug Mart
Category: otc | Type: Human OTC Drug Label
Date: 20130618

ACTIVE INGREDIENTS: ACETAMINOPHEN 500 mg/1 1; DIPHENHYDRAMINE HYDROCHLORIDE 25 mg/1 1
INACTIVE INGREDIENTS: CROSCARMELLOSE SODIUM; FD&C BLUE NO. 1; CELLULOSE, MICROCRYSTALLINE; STEARIC ACID; TITANIUM DIOXIDE; POLYETHYLENE GLYCOLS; HYPROMELLOSES

ACTIVE INGREDIENT(S)

Acetaminophen 500 mg

Diphenhydramine HCl 25 mg

PURPOSE

Pain reliever

Nighttime sleep aid

USE(S)

Temporary relief of occasional headaches and minor aches and pains with accompanying sleeplessness

WARNINGS

Liver warning

This product contains acetaminophen. Severe liver damage may occur if you take

- more than 4,000 mg of acetaminophen in 24 hours
- with other drugs containing acetaminophen
- 3 or more alcoholic drinks every day while using this product

DO NOT USE

- With any other drug containing acetaminophen (prescription or nonprescription). If you are not sure whether a drug contains acetaminophen, ask a doctor or pharmacist.
- with any product containing diphenhydramine, even one used on skin
- in children under 12 years of age
- if you have ever had an allergic reaction to this product or any of its ingredients

ASK A DOCTOR BEFORE USE IF

You have

- liver disease
- a breathing problem such as emphysema or chronic bronchitis
- trouble urinating due to an enlarged prostate gland
- glaucoma

ASK A DOCTOR OR PHARMACIST BEFORE USE IF

- taking the blood thinning drug warfarin
- taking sedatives or tranquilizers

WHEN USING THIS PRODUCT

- drowsiness will occur
- avoid alcoholic drinks
- do not drive a motor vehicle or operate machinery

STOP USE AND ASK DOCTOR IF

- Sleeplessness persists continuously for more than 2 weeks. Insomnia may be a symptom of serious underlying medical illness.
- pain gets worse or lasts more than 10 days
- fever gets worse or lasts more than 3 days
- redness or swelling is present
- new symptoms occur

These could be signs of a serious condition.

PREGNANCY/BREASTFEEDING

Ask a health professional before use.

KEEP OUT OF REACH OF CHILDREN

Overdose warning

Taking more than the recommended dose (overdose) may cause liver damage. In case of overdose, get medical help or contact a Poison Control Center right away. (1-800-222-1222) Quick medical attention is critical for adults as well as for children even if you do not notice any signs or symptoms.

DIRECTIONS

- do not take more than directed (see overdose warning)

adults and children 12 years and over | - take 2 caplets at bedtime - do not take more than 2 caplets of this product in 24 hours
children under 12 years | do not use this adult product in children under 12 years of age; this will provide more than the recommended dose (overdose) and may cause liver damage

STORAGE

- store between 20-25°C (68-77°F)
- do not use is carton is opened, or neck wrap or foil inner seal imprinted "Safety Seal®" is broken or missing
- see end panel for lot number and expiration date

INACTIVE INGREDIENT SECTION

Croscarmellose sodium, FD&C blue #1, Hypromellose, Microcrsytalline cellulose, Polyethylene glycol, Stearic acid, Titanium Dioxide.

PRINCIPAL DISPLAY PANEL

Carton Label PDP

Drug mart

EXTRA STRENGTH

PAIN RELIEF PM

NON-ASPIRIN PAIN RELIEVER/ SLEEP AID

CAPLETS

ACETAMINOPHEN 500 mg

DIPHENHYDRAMINE HCl 25 mg

50 COATED CAPLETS

Bottle Label PDP

Drug mart

EXTRA STRENGTH

PAIN RELIEF PM

NON-ASPIRIN PAIN RELIEVER/ SLEEP AID

CAPLETS

ACETAMINOPHEN 500 mg

DIPHENHYDRAMINE HCl 25 mg

50 COATED CAPLETS

CARTON LABEL PDP

Drug mart

EXTRA STRENGTH

PAIN RELIEF PM

NON-ASPIRIN PAIN RELIEVER/ SLEEP AID

CAPLETS

ACETAMINOPHEN 500 mg

DIPHENHYDRAMINE HCl 25 mg

100 COATED CAPLETS

Bottle Label PDP

Drug mart

EXTRA STRENGTH

PAIN RELIEF PM

NON-ASPIRIN PAIN RELIEVER/ SLEEP AID

CAPLETS

ACETAMINOPHEN 500 mg

DIPHENHYDRAMINE HCl 25 mg

100 COATED CAPLETS

Bottle Label PDP

Drug mart

EXTRA STRENGTH

PAIN RELIEF PM

NON-ASPIRIN PAIN RELIEVER/ SLEEP AID

CAPLETS

ACETAMINOPHEN 500 mg

DIPHENHYDRAMINE HCl 25 mg

300 COATED CAPLETS